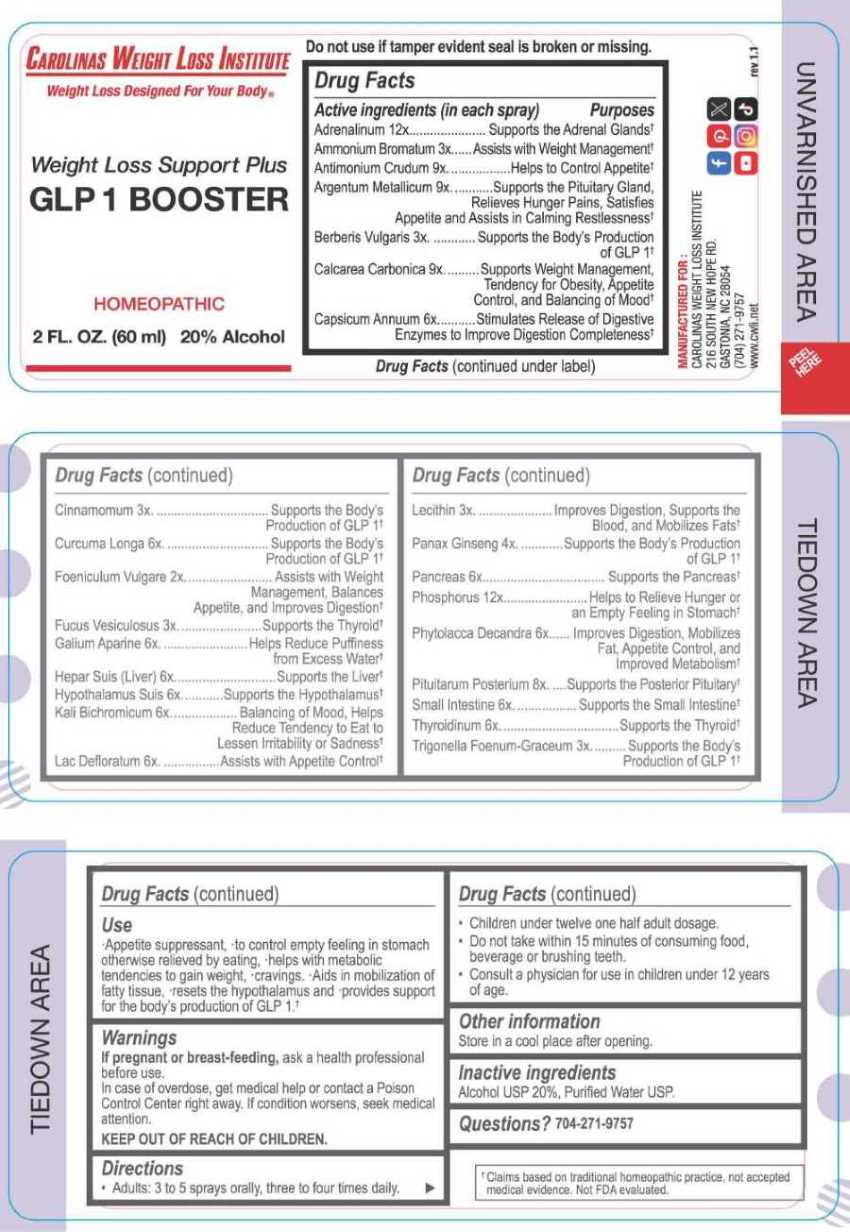 DRUG LABEL: Weight Loss support Plus - GLP 1 Booster
NDC: 83014-0100 | Form: SPRAY
Manufacturer: Carolinas Weight Loss Institute
Category: homeopathic | Type: HUMAN OTC DRUG LABEL
Date: 20260129

ACTIVE INGREDIENTS: FOENICULUM VULGARE FRUIT 2 [hp_X]/1 mL; AMMONIUM BROMIDE 3 [hp_X]/1 mL; BERBERIS VULGARIS ROOT BARK 3 [hp_X]/1 mL; CINNAMON 3 [hp_X]/1 mL; FUCUS VESICULOSUS 3 [hp_X]/1 mL; EGG PHOSPHOLIPIDS 3 [hp_X]/1 mL; FENUGREEK SEED 3 [hp_X]/1 mL; ASIAN GINSENG 4 [hp_X]/1 mL; CAPSICUM 6 [hp_X]/1 mL; TURMERIC 6 [hp_X]/1 mL; GALIUM APARINE WHOLE 6 [hp_X]/1 mL; PORK LIVER 6 [hp_X]/1 mL; SUS SCROFA HYPOTHALAMUS 6 [hp_X]/1 mL; POTASSIUM DICHROMATE 6 [hp_X]/1 mL; SKIM MILK 6 [hp_X]/1 mL; SUS SCROFA PANCREAS 6 [hp_X]/1 mL; PHYTOLACCA AMERICANA ROOT 6 [hp_X]/1 mL; SUS SCROFA INTESTINAL MUCOSA 6 [hp_X]/1 mL; BOS TAURUS PITUITARY GLAND, POSTERIOR 8 [hp_X]/1 mL; THYROID, BOVINE 6 [hp_X]/1 mL; ANTIMONY TRISULFIDE 9 [hp_X]/1 mL; SILVER 9 [hp_X]/1 mL; OYSTER SHELL CALCIUM CARBONATE, CRUDE 9 [hp_X]/1 mL; EPINEPHRINE 12 [hp_X]/1 mL; PHOSPHORUS 12 [hp_X]/1 mL
INACTIVE INGREDIENTS: WATER; ALCOHOL

DRUG FACTS:

ACTIVE INGREDIENTS:

(in each spray) Adrenalinum 12X, Ammonium Bromatum 3X, Antimonium Crudum 9X, Argentum Metallicum 9X, Berberis Vulgaris 3X, Calcarea Carbonica 9X, Capsicum Annuum 6X, Cinnamomum 3X, Curcuma Longa 6X, Foeniculum Vulgare 2X, Fucus Vesiculosus 3X, Galium Aparine 6X, Hepar Suis (Liver) 6X, Hypothalamus Suis 6X, Kali Bichromicum 6X, Lac Defloratum 6X, Lecithin 3X, Panax Ginseng 4X, Pancreas 6X, Phosphorus 12X, Phytolacca Decandra 6X, Pituitarum Posterium 8X, Small Intestine 6X, Thyroidinum 6X, Trigonella Foenum-Graecum 3X.

PURPOSE:

Adrenalinum – Supports the Adrenal Glands,† Ammonium Bromatum – Assists with Weight Management,† Antimonium Crudum – Helps to Control Appetite,† Argentum Metallicum – Supports the Pituitary Gland, Relieves Hunger Pains, Satisfies Appetite and Assists in Calming Restlessness,† Berberis Vulgaris – Supports the Body’s Production of GLP 1,† Calcarea Carbonica – Supports Weight Management, Tendency for Obesity, Appetite Control, and Balancing of Mood,† Capsicum Annuum – Stimulates Release of Digestive Enzymes to Improve Digestion Completeness,† Cinnamomum – Supports the Body’s Production of GLP 1,† Curcuma Longa - Supports the Body’s Production of GLP 1,† Foeniculum Vulgare – Assists with Weight Management, Balances Appetite, and Improves Digestion,† Fucus Vesiculosus – Supports the Thyroid,† Galium Aparine – Helps Reduce Puffiness from Excess Water,† Hepar Suis (Liver) – Supports the Liver,† Hypothalamus Suis – Supports the Hypothalamus,† Kali Bichromicum – Balancing of Mood, Helps Reduce Tendency to Eat to Lessen Irritability or Sadness,† Lac Defloratum – Assists with Appetite Control,† Lecithin – Improves Digestion, Supports the Blood, and Mobilizes Fats,† Panax Ginseng – Supports the Body’s Production of GLP 1,† Pancreas – Supports the Pancreas,† Phosphorus – Helps to Relieve Hunger or an Empty Feeling in Stomach,† Phytolacca Decandra – Improves Digestion, Mobilizes Fat, Appetite Control, and Improved Metabolism,† Pituitarum Posterium – Supports the Posterior Pituitary,† Small Intestine – Supports the Small Intestine,† Thyroidinum – Supports the Thyroid,† Trigonella Foenum-Graecum 3X – Supports the Body’s Production of GLP 1†

†Claims based on traditional homeopathic practices, not accepted medical evidence. Not FDA evaluated.

USES:

Appetite suppressant to control empty feeling in stomach otherwise relieved by eating, helps with metabolic tendencies to gain weight, cravings. Aids in mobilization of fatty tissue, resets the hypothalamus and provides support for the body's production of GLP 1.†

†Claims based on traditional homeopathic practice, not accepted medical evidence. Not FDA evaluated.

WARNINGS:

If pregnant or breast-feeding, ask a health professional before use.

In case of overdose, get medical help or contact a Poison Control Center right away.

If condition worsens, seek medical attention.

KEEP OUT OF REACH OF CHILDREN

Do not use if tamper evident seal is broken or missing.

Store in a cool place after opening

KEEP OUT OF REACH OF CHILDREN:

In case of overdose, get medical help or contact a Poison Control Center right away.

DIRECTIONS:

• Adults: 3 to 5 sprays orally, three to four times daily.

• Children under twelve, one half adult dosage.

• Do not take within 15 minutes of consuming food, beverage or brushing teeth.

• Consult a physician for use in children under 12 years of age.

INACTIVE INGREDIENTS:

Alcohol USP 20%, Purified Water USP.

QUESTIONS:

MANUFACTURED FOR:

CAROLINAS WEIGHT LOSS INSTITUTE

216 SOUTH NEW HOPE RD.

GASTONIA, NC 28054

(704) 271-9757

www.cwli.net

PACKAGE LABEL DISPLAY:

CAROLINAS WEIGHT LOSS INSTITUTE

Weight Loss Designed For Your Body®

Weight Loss Support Plus

GLP 1 Booster

HOMEOPATHIC

2 FL. OZ. (60 ml)